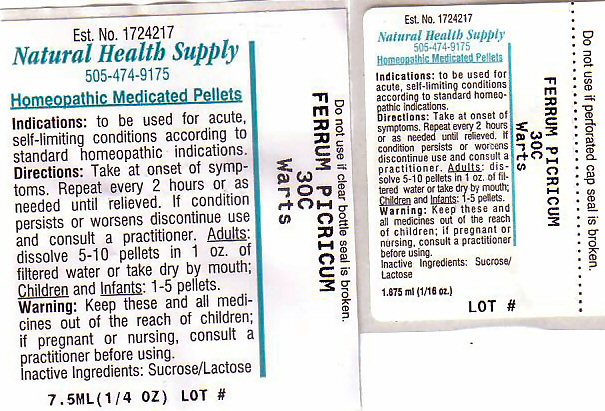 DRUG LABEL: WARTS
NDC: 64117-230 | Form: PELLET
Manufacturer: Natural Health Supply
Category: homeopathic | Type: HUMAN OTC DRUG LABEL
Date: 20211115

ACTIVE INGREDIENTS: FERRIC PICRATE 30 [hp_C]/1 mL
INACTIVE INGREDIENTS: LACTOSE; SUCROSE

Indications

Indications: To be used for acute self-limiting conditions according to standard homeopathic indications

Active Ingredient

FERRUM PICRICUM

Directions

Take at onset of symptoms. Repeat every 2 hours or as needed until relieved. If condition persists or worsens discontinue use and consult a practitioner.

Adults: dissolve 5-10 pellets in 1 oz. of filtered water or take dry by mouth. Children and infants: 1-5 pellets.

Keep Out of Reach of Children

Keep these and all medications out of the reach of children.

Warning

If pregnant or nursing, consult a practitioner before using.

Inactive Ingredients - Lactose, Sucrose

Purpose

Purpose: WARTS

Package Label

Est. No. 1724217
Natural Health Supply
505-474-9175
Homeopathic Medicated Pellets
Do not use if clear bottle seal is broken. Do not use if perforated cap seal is broken.

FERRUM PICRICUM 30CC

Lot #__________________

res